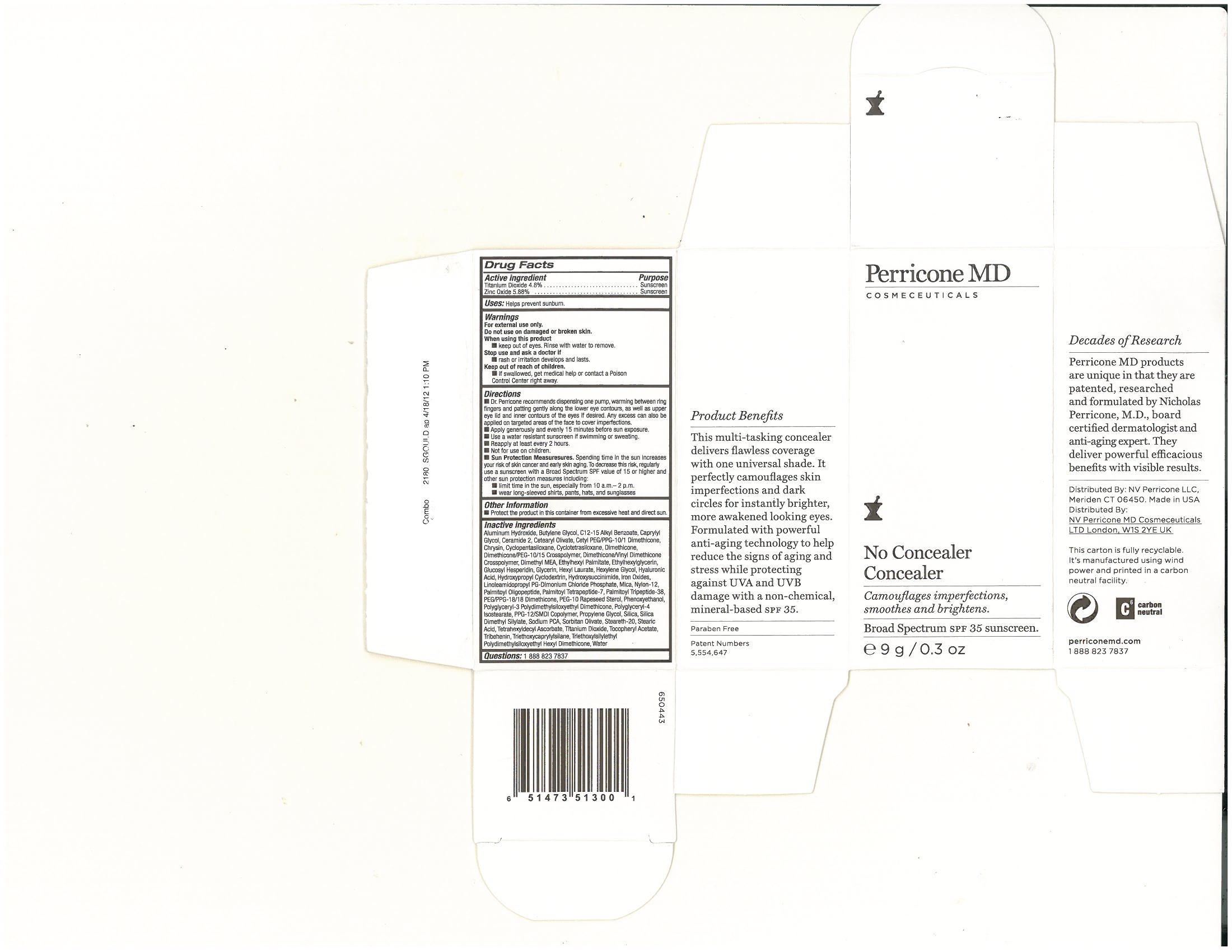 DRUG LABEL: No Concealer Concealer
NDC: 62742-4059 | Form: CREAM
Manufacturer: Allure Labs, Inc
Category: otc | Type: HUMAN OTC DRUG LABEL
Date: 20131209

ACTIVE INGREDIENTS: Titanium Dioxide 48 mg/1 g; Zinc Oxide 58.8 mg/1 g
INACTIVE INGREDIENTS: Aluminum Hydroxide; Butylene Glycol; ALKYL (C12-15) BENZOATE; CAPRYLYL GLYCOL ; CERAMIDE 2; CETEARYL OLIVATE ; CETYL PEG/PPG-10/1 DIMETHICONE (HLB 4) ; CHRYSIN ; CYCLOMETHICONE 5; DIMETHICONE; DIMETHICONE/VINYL DIMETHICONE CROSSPOLYMER (SOFT PARTICLE) ; DEANOL ; ETHYLHEXYL PALMITATE; ETHYLHEXYLGLYCERIN; GLUCOSYL HESPERIDIN ; GLYCERIN ; HEXYL LAURATE ; HEXYLENE GLYCOL; HYALURONIC ACID ; HYDROXYPROPYL .BETA.-CYCLODEXTRIN; N-HYDROXYSUCCINIMIDE; FERRIC OXIDE RED  ; LINOLEAMIDOPROPYL PG-DIMONIUM CHLORIDE PHOSPHATE; MICA  ; NYLON-12 ; PALMITOYL OLIGOPEPTIDE ; PALMITOYL TETRAPEPTIDE-7 ; PALMITOYL LYSYLDIOXYMETHIONYLLYSINE; PEG/PPG-18/18 DIMETHICONE ; PEG-10 RAPESEED STEROL; PHENOXYETHANOL ; POLYGLYCERYL-4 ISOSTEARATE ; PPG-12/SMDI COPOLYMER; PROPYLENE GLYCOL ; SILICON DIOXIDE; SODIUM PYRROLIDONE CARBOXYLATE; SORBITAN OLIVATE ; STEARETH-20; TETRAHEXYLDECYL ASCORBATE ; .ALPHA.-TOCOPHEROL ACETATE ; TRIBEHENIN  ; STEARIC ACID ; WATER

Drug Facts

Active Ingredients:

Titanium Dioxide 4.8%

Zinc Oxide 5.88%

PURPOSE:

Sunscreen

Uses:

- Helps prevent sunburn

Warning:

- For External Use Only

- Do not use on damaged or broken skin

WHEN USING THIS PRODUCT:

- keep out of eyes. Rinse with water to remove

STOP USE AND ASK DOCTOR IF

rash or irritation develops and lasts

KEEP OUT OF REACH OF CHILDREN

- if swallowed get medical help or contact a poison control center right away

DIRECTIONS:

Dr. Perricone recommends dispensing one pump, warmimg between ring fingers and patting gently along the lower eye contours, as well as upper eye lid and inner contours of eyes if desired. Any excess can also be applied on targeted areas of the face to cover imperfections.Apply generously and evenly 15 minutes before sun exposureUse a water resistant sunscreen if swimming or sweatingReapply atleast every two hoursNot for use on children

STORAGE AND HANDLING

Protect the product in this container from excessive heat and direct sun

INACTIVE INGREDIENT

Aluminum Hydroxide, Butylene Glycol, C12-15 Alkyl benzoate, Caprylyl Glyohol, Ceramide 2, Cetearyl Olivate, Cetyl PEG/PPG-10/1 Dimethicone, Chrysin, Cyclopentasiloxane, Cyclotetrasiloxane, Dimethicone, Dimethicone/PEG-10/15 Crosspolymer, Dimethicone/Vinyl Dimethicone Crosspolymer, Dimethyl MEA, Ethylhexylglycerin, Glucosyl Herperidin, Glycerin, Hexyl Laurate, Hexylene Glyol, Hyaluronic Acid, Hydroxypropyl Cyclodextrin, Hydoxysuccinimde, Iron Oxides, Linoleamidopropyl PG-Dimonium Chloride Phophate, Mica, Nylon-12, Palmitoyl Oligopeptide, Palmitoyl Terapeptide-7, Palmitoyl Tripeptide-38, PEG/18/18 Dimethicone, PEG-10 Rapeseed Sterol, Phenoxyethanol, Polyglyceryl-3 Polydimethylsiloxyehtyl Dimethicone, Polyglyceryl-4, Isostearate, PPG-12/SMDI Copoloymer, Propylene Glycol, Silica, Silica Dimehtyl Silylate, Sodium PCA, Sorbiana Olivate, Streareth-20, Stearic Acid, Tetrahexyldecy Ascorbate, Titanium Dioxide, Tocopheryl Acetate, Tribehenin, Triethoxycaprylysilane, Triethoxylsilylethyl Polydimehtylsiloxyehtyl Hexyl Dimethicone, Water.

PACKAGE LABEL

Distributed By (US): NV Perricone LLC Meriden CT 06450 Made in USA

Distributed By (UK): NV Perricone MD Cosmeceuticals Ltd London W1S 2YE UK

www.perriocnemd.com 1-888-823-7837